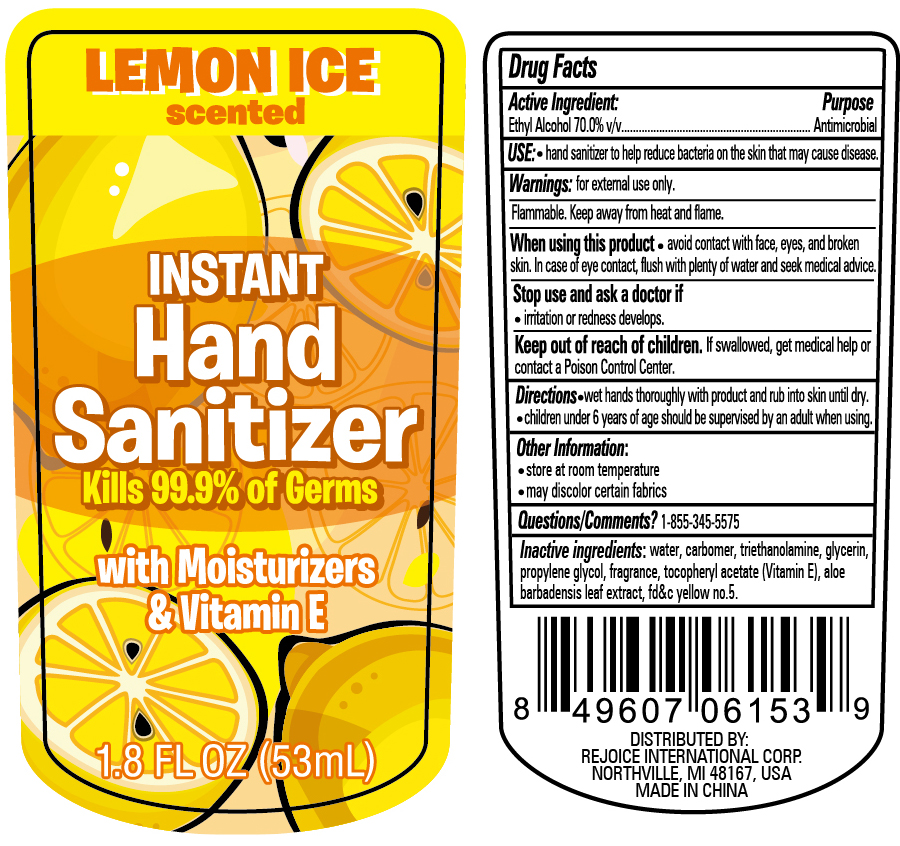 DRUG LABEL: Hand Sanitizer 1.8 oz Lemon Ice
NDC: 57337-110 | Form: LIQUID
Manufacturer: Ningbo Rejoice International
Category: otc | Type: HUMAN OTC DRUG LABEL
Date: 20250213

ACTIVE INGREDIENTS: ALCOHOL 70 mL/100 mL
INACTIVE INGREDIENTS: GLYCERIN; WATER; ALPHA-TOCOPHEROL ACETATE; ALOE VERA LEAF; FD&C YELLOW NO. 5; TROLAMINE; PROPYLENE GLYCOL; CARBOMER HOMOPOLYMER, UNSPECIFIED TYPE

Hand Sanitizer Spray 1.8oz with lemon ice

ACTIVE INGREDIENT

Ethyl Alcohol 70.0% v/v

PURPOSE

Antimicrobial

INDICATIONS AND USAGE

Hand sanitizer to help reduce bacteria on the skin that may cause disease

WARNINGS

For external use only.

Flammable, keep away from fire or flame

When using this product

- avoid contact with face, eyes, and broken skin. In case of eye contact, flush with plenty of water and seek medical advice

Stop use and ask a doctor

- if irritation and redness develop

Keep out of reach of children. If swallowed, get medical help or contact a Poison Control Center.

Directions

- Wet hands thoroughly with product and rub into skin until dry.
- Children under 6 years of age should be supervised by an adult when using

Other Information

- store at room temperature
- may discolor certain fabrics

INACTIVE INGREDIENT

water, carbomer, triethanolamine, glycerin, propylene glycol, fragrance, tocopheryl acetate (Vitamin E), aloe barbadensis leaf extract, fd&c yellow no. 5